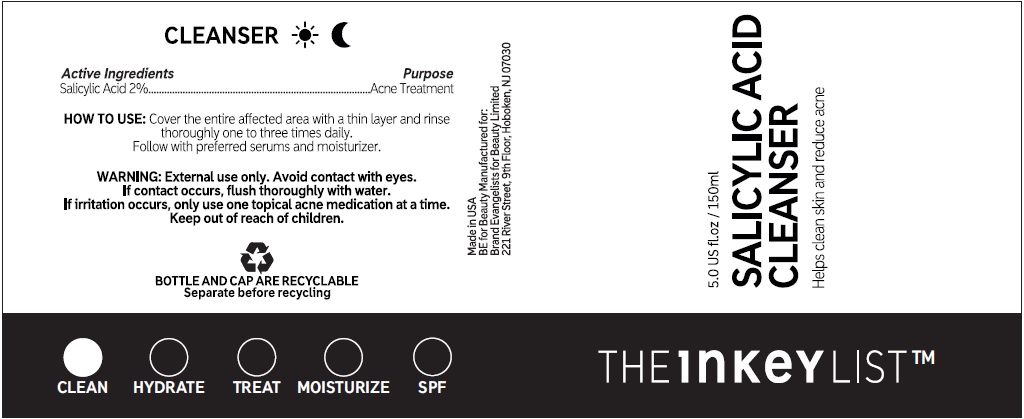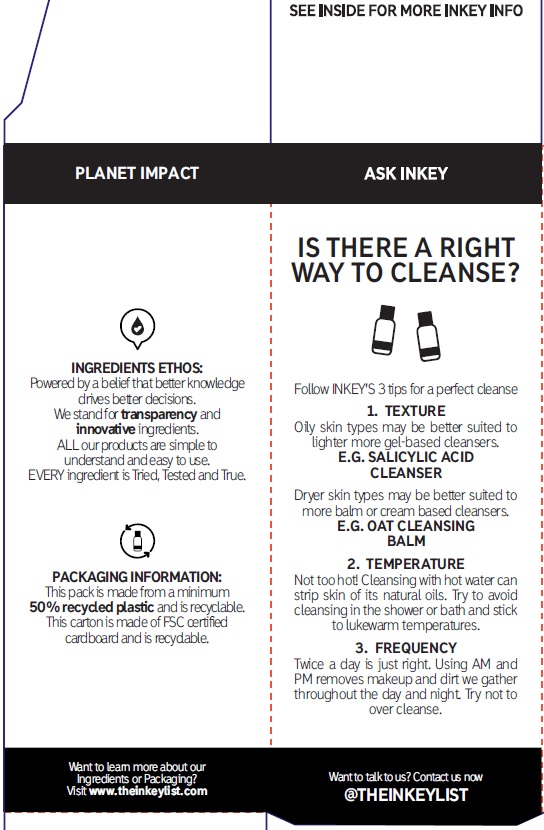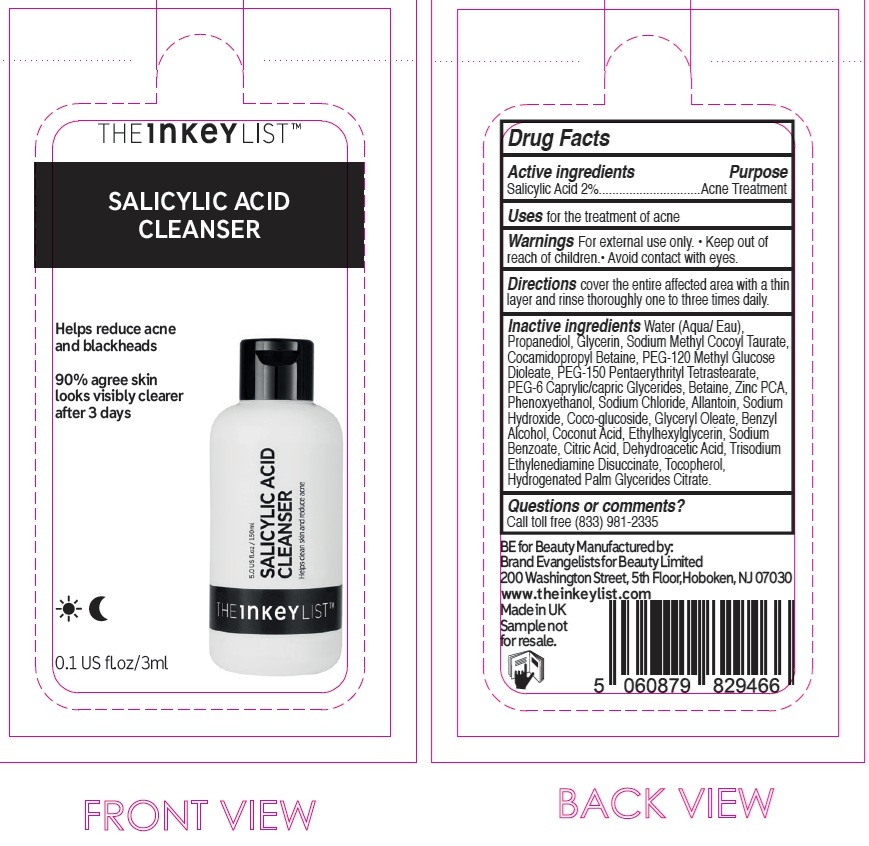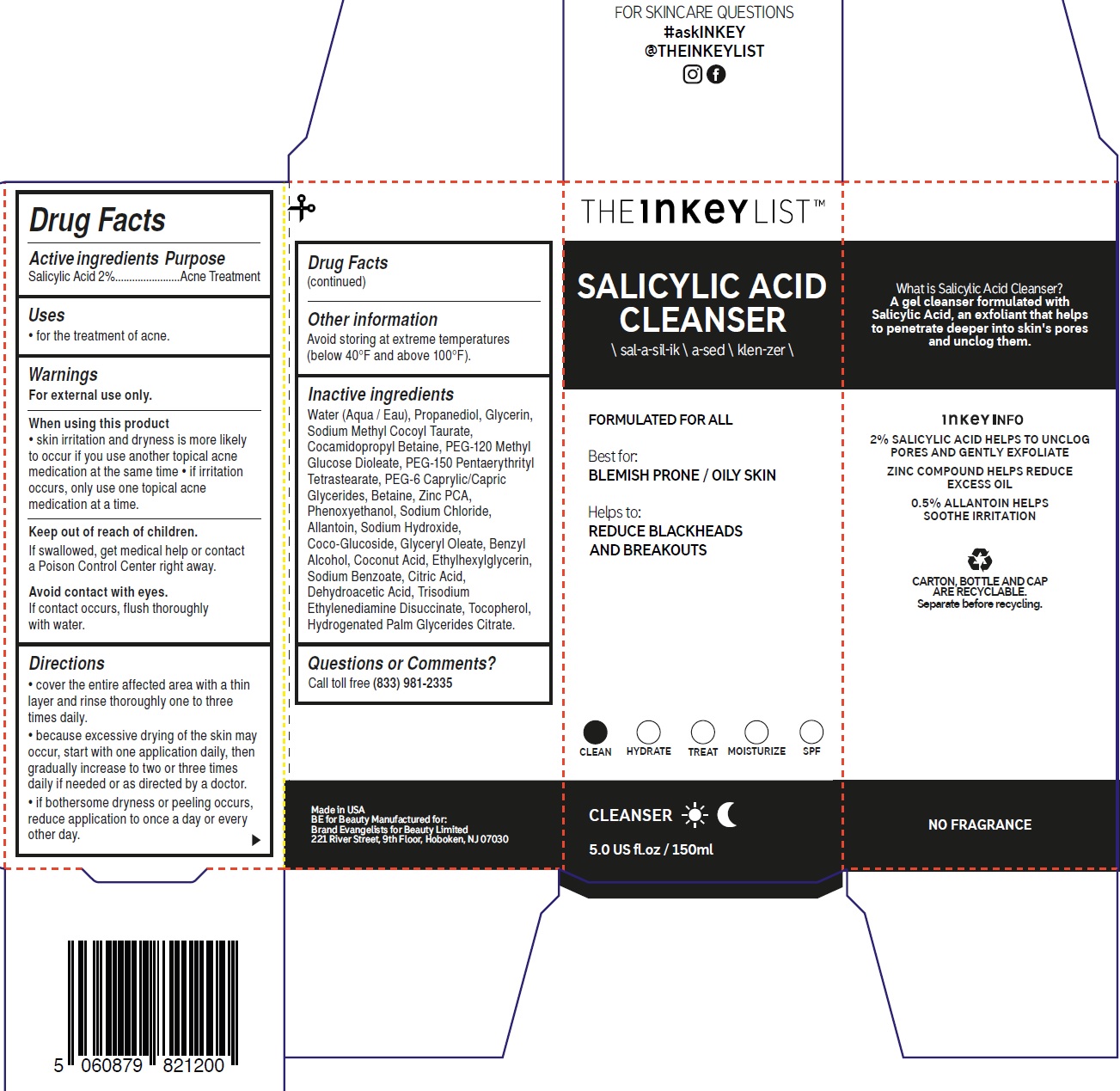 DRUG LABEL: The INKEY List Salicylic Acid Cleanser
NDC: 81136-019 | Form: GEL
Manufacturer: Brand Evangelists for Beauty Ltd
Category: otc | Type: HUMAN OTC DRUG LABEL
Date: 20250307

ACTIVE INGREDIENTS: SALICYLIC ACID 20 mg/1 mL
INACTIVE INGREDIENTS: HYDROGENATED PALM GLYCERIDES CITRATE; WATER; PROPANEDIOL; GLYCERIN; SODIUM METHYL COCOYL TAURATE; COCAMIDOPROPYL BETAINE; PEG-120 METHYL GLUCOSE DIOLEATE; PEG-150 PENTAERYTHRITYL TETRASTEARATE; PEG-6 CAPRYLIC/CAPRIC GLYCERIDES; BETAINE; ZINC PIDOLATE; PHENOXYETHANOL; SODIUM CHLORIDE; ALLANTOIN; SODIUM HYDROXIDE; COCO GLUCOSIDE; GLYCERYL OLEATE; BENZYL ALCOHOL; COCONUT ACID; ETHYLHEXYLGLYCERIN; SODIUM BENZOATE; CITRIC ACID MONOHYDRATE; DEHYDROACETIC ACID; TRISODIUM ETHYLENEDIAMINE DISUCCINATE; TOCOPHEROL

The INKEY List Salicylic Acid Cleanser

Active ingredients

Salicylic Acid 2%

Purpose

Acne Treatment

Uses

• for the treatment of acne.

Warnings

For external use only.

When using this product

• skin irritation and dryness is more likely to occur if you use another topical acne medication at the same time • if irritation occurs, only use one topical acne medication at a time.

Keep out of reach of children.

If swallowed, get medical help or contact a Poison Control Center right away.

If contact occurs, flush thoroughly with water. Avoid contact with eyes.

Directions

• cover the entire affected area with a thin layer and rinse thoroughly one to three times daily. • because excessive drying of the skin may occur, start with one application daily, then gradually increase to two or three times daily if needed or as directed by a doctor. • if bothersome dryness or peeling occurs, reduce application to once a day or every other day.

Other information

Avoid storing at extreme temperatures (below 40°F and above 100°F).

Inactive ingredients

Water (Aqua / Eau), Propanediol, Glycerin, Sodium Methyl Cocoyl Taurate, Cocamidopropyl Betaine, PEG-120 Methyl Glucose Dioleate, PEG-150 Pentaerythrityl Tetrastearate, PEG-6 Caprylic/Capric Glycerides, Betaine, Zinc PCA, Phenoxyethanol, Sodium Chloride, Allantoin, Sodium Hydroxide, Coco-Glucoside, Glyceryl Oleate, Benzyl Alcohol, Coconut Acid, Ethylhexylglycerin, Sodium Benzoate, Citric Acid, Dehydroacetic Acid, Trisodium Ethylenediamine Disuccinate, Tocopherol, Hydrogenated Palm Glycerides Citrate.

Questions or Comments?

Call toll free (833) 981-2335